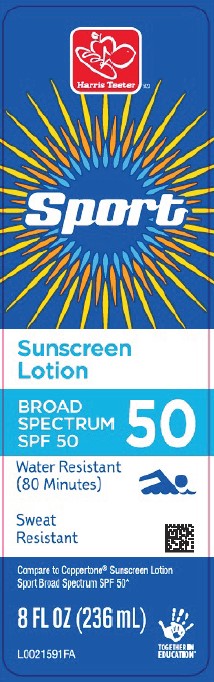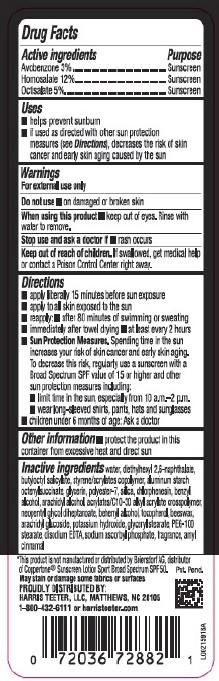 DRUG LABEL: Sport Sunscreen SPF 50
NDC: 72036-940 | Form: LOTION
Manufacturer: HARRIS TEETER
Category: otc | Type: HUMAN OTC DRUG LABEL
Date: 20260204

ACTIVE INGREDIENTS: AVOBENZONE 30 mg/1 mL; HOMOSALATE 120 mg/1 mL; OCTISALATE 50 mg/1 mL
INACTIVE INGREDIENTS: DIETHYLHEXYL 2,6-NAPHTHALATE; BUTYLOCTYL SALICYLATE; STYRENE/ACRYLAMIDE COPOLYMER (500000 MW); ALUMINUM STARCH OCTENYLSUCCINATE; GLYCERIN; POLYESTER-7; SILICON DIOXIDE; CHLORPHENESIN; BENZYL ALCOHOL; WATER; ARACHIDYL ALCOHOL; CARBOMER COPOLYMER TYPE B (ALLYL PENTAERYTHRITOL CROSSLINKED); NEOPENTYL GLYCOL DIHEPTANOATE; DOCOSANOL; TOCOPHEROL; YELLOW WAX; ARACHIDYL GLUCOSIDE; POTASSIUM HYDROXIDE; GLYCERYL MONOSTEARATE; PEG-100 STEARATE; EDETATE DISODIUM ANHYDROUS; SODIUM ASCORBYL PHOSPHATE; .ALPHA.-AMYLCINNAMALDEHYDE

Harris Teeter D40.000/D40AA
Sport Sunscreen Lotion SPF 50

Active ingredients

Avobenzone 3%

Homosalate 12%

Octisalate 5%

Purpose

Sunscreen

Uses

- helps prevent sunburn
- if used as directed with other sun protections measures (see Directions), decreases the risk of skin cancer and early skin aging caused by the sun

Warnings

For external use only

Do not use

- on damaged or broken skin

When using this product

- keep out of eyes. Rinse with water to remove.

Stop use and ask a doctor if

- rash occurs

Keep out of reach of children.

If swallowed, get medical help or contact a Poison Control Center right away.

Directions

- apply liberally 15 minutes before sun exposure
- apply to all skin exposed to the sun
- reapply:
- after 80 minutes of swimming or sweating
- immediately after towel drying
- at least every 2 hours
- Sun Protection Measures. Spending time in the sun increases your risk of skin cancer and early skin aging. To decrease this risk, regularly use a sunscreen with a Broad Spectrum SPF value of 15 or higher and other sun protection measures including:
- limit time in the sun, especially from 10 a.m.–2 p.m.
- wear long-sleeved shirts, pants, hats and sunglasses
- children under 6 months of age: Ask a doctor

Other information

- Protect the product in this container from excessive heat and direct sun

Inactive ingredients

water, diethylhexyl 2,6-naphthalate, butyloctyl salicylate, styrene/acrylates copolymer, aluminum starch octenylsuccinate, glycerin, polyester-7, silica, chlorphenesin, benzyl alcohol, arachidyl alcohol, acrylates/C10-30 alkyl acrylate crosspolymer, neopentyl glycol diheptanoate, behenyl alcohol, tocopherol, beeswax, arachidyl glucoside, potassium hydroxide, glyceryl stearate, PEG-100 stearate, disodium EDTA, sodium ascorbyl phosphate, fragrance, amyl cinnamal

Disclaimers

*This product is not manufactured or distributed by Beiersdorf AG, distributor of Coppertone®Sunscreen Lotion Sport Broad Spectrum SPF 50.

May stain or damage some fabrics or surfaces.

Adverse Reaction

PROUDLY DISTRIBUTED BY:

HARRIS TEETER, LLC, MATTHEWS, NC 28105

1-800-432-6111 or harristeeter.com

Principal display panel

Harris Teeter™

Sport

Sunscreen Lotion

BROAD SPECTRUM SPF 50

50

Water Resistant (80 minutes)

Sweat Resistant

Compare to Coppertone®Sunscreen Lotion Sport Broad Spectrum SPF 50*

8 FL OZ (236 mL)

TOGETHER IN EDUCATION